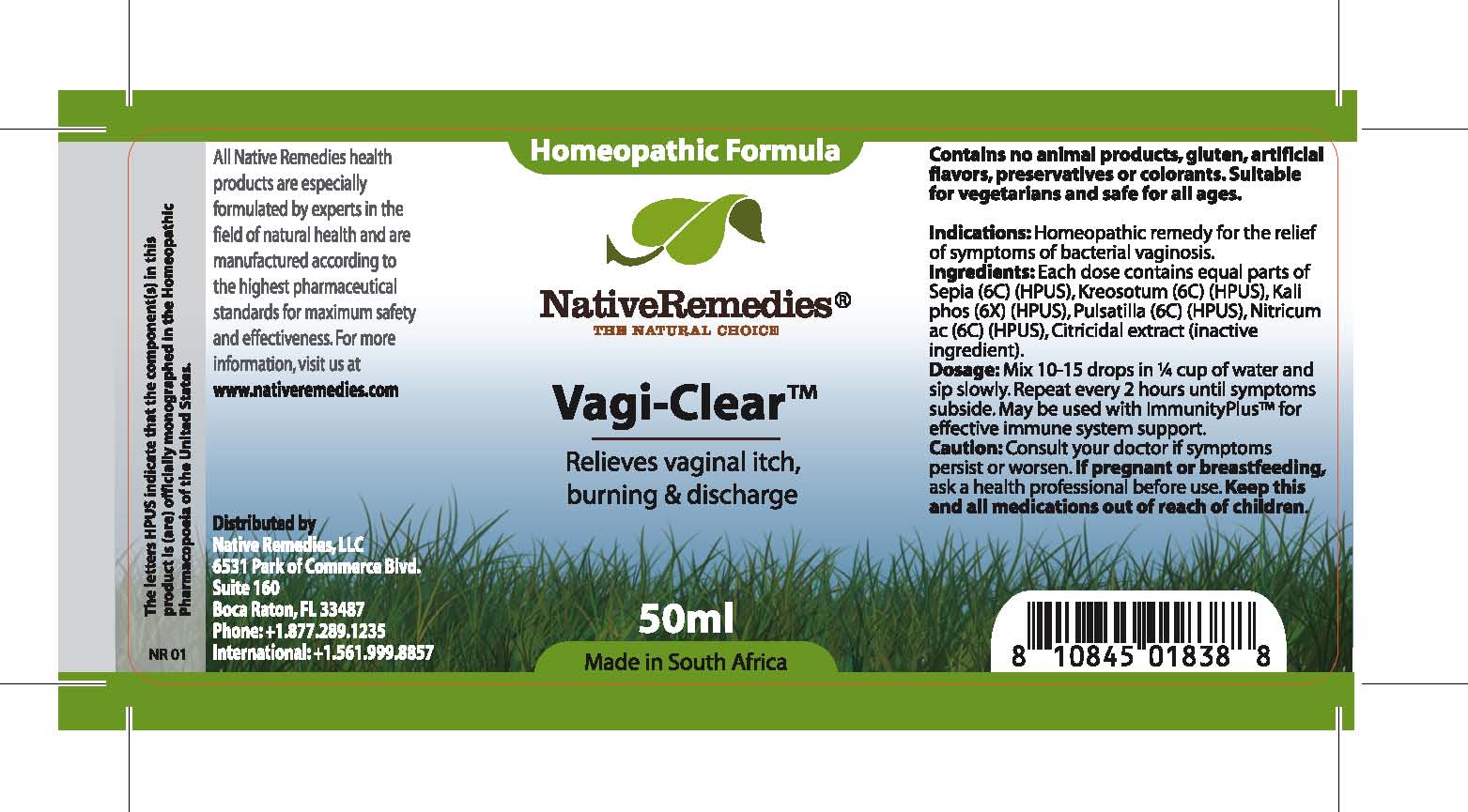 DRUG LABEL: Vagi-Clear
NDC: 68647-201 | Form: TINCTURE
Manufacturer: Feelgood Health
Category: homeopathic | Type: HUMAN OTC DRUG LABEL
Date: 20110707

ACTIVE INGREDIENTS: SEPIA OFFICINALIS JUICE 6 [hp_C]/40 mL; LARREA TRIDENTATA TOP 6 [hp_C]/40 mL; POTASSIUM PHOSPHATE, DIBASIC 6 [hp_X]/40 mL; PULSATILLA PATENS 6 [hp_C]/40 mL; NITRIC ACID 6 [hp_C]/40 mL
INACTIVE INGREDIENTS: CITRUS PARADISI SEED 0.03 mL/50 mL; WATER 0.03 mL/50 mL

VAGI-CLEAR

PURPOSE

Relieves vaginal itch, burning and discharge

INDICATIONS AND USAGE

Indications: Homeopathic remedy for the relief of symptoms of bacterial vaginosis.

DOSAGE AND ADMINISTRATION

Dosage: Mix 10-15 drops in ¼ cup of water and sip slowly. Repeat every 2 hours until symptoms subside. May be used with ImmunityPlus™ for effective immune system support.

GENERAL PRECAUTIONS

Caution: Consult your doctor if symptoms persist or worsen. Keep this and all medications out of reach of children.

ACTIVE INGREDIENT

Ingredients: Each dose contains equal parts of Sepia (6C) (HPUS), Kreosotum (6C) (HPUS), Kali phos (6X) (HPUS), Pulsatilla (6C) (HPUS), Nitricum ac (6C) (HPUS)

Citricidal extract (inactive ingredient).

PREGNANCY

If pregnant or breastfeeding, ask a health professional before use.

WARNINGS

Contains no animal products, gluten, artificial flavors, preservatives or colorants. Suitable for vegetarians and safe for all ages.

PATIENT COUNSELING INFORMATION

All Native Remedies health products are especially formulated by experts in the field of natural health and are manufactured according to the highest pharmaceutical standards for maximum safety and effectiveness. For more information, visit us at www.nativeremedies.com

Distributed by

Native Remedies, LLC

6531 Park of Commerce Blvd.

Suite 160

Boca Raton, FL 33487

Phone: 1.877.289.1235

International: + 1.561.999.8857

The letters HPUS indicate that the component(s) in this product is (are) officially monographed in the Homeopathic Pharmacopoeia of the United States.

KEEP OUT OF REACH OF CHILDREN

Keep this and all medications out of reach of children.